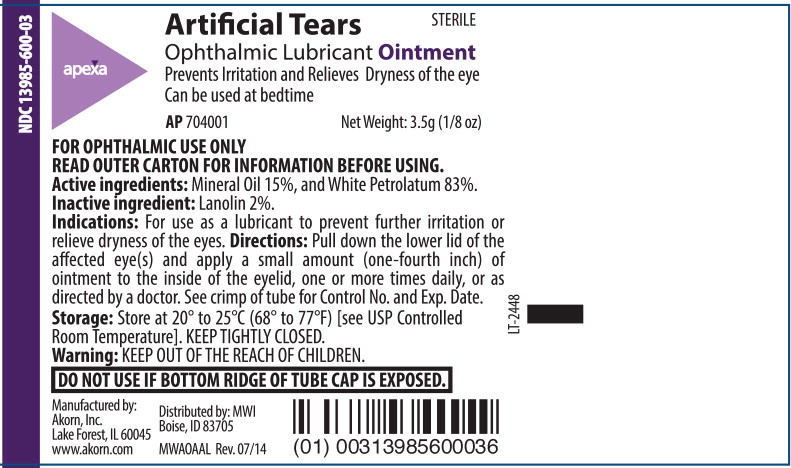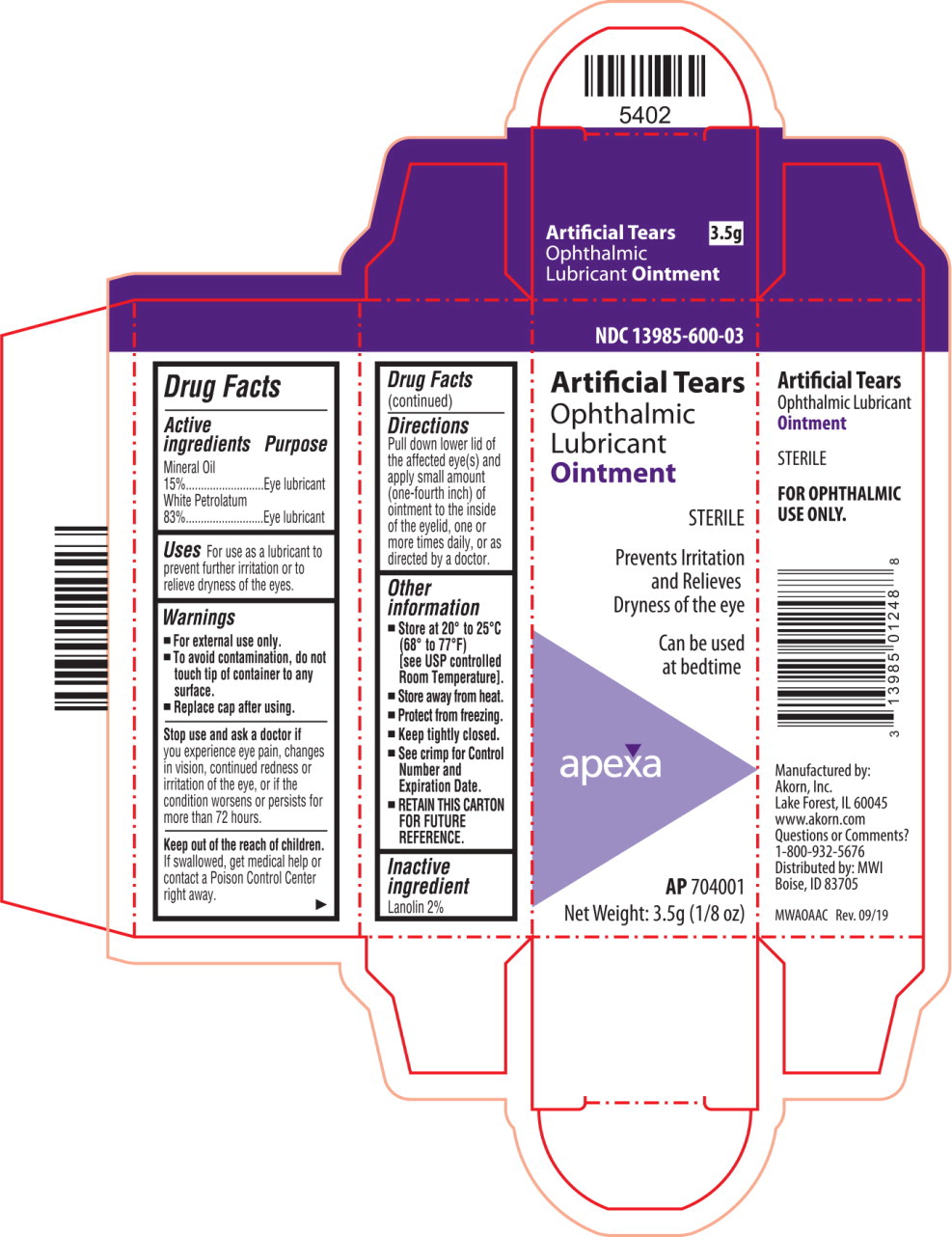 DRUG LABEL: Artificial Tears
NDC: 13985-600 | Form: OINTMENT
Manufacturer: MWI
Category: otc | Type: HUMAN OTC DRUG LABEL
Date: 20220208

ACTIVE INGREDIENTS: Mineral Oil 150 mg/1 g; Petrolatum 830 mg/1 g
INACTIVE INGREDIENTS: Lanolin

Drug Facts

Active ingredients

Mineral Oil
15%

White Petrolatum
83%

Purpose

Eye lubricant

Eye lubricant

Uses

For use as a lubricant to prevent further irritation or to relieve dryness of the eyes.

Warnings

- For external use only.
- To avoid contamination, do not touch tip of container to any surface.
- Replace cap after using.

Stop use and ask a doctor if you experience eye pain, changes in vision, continued redness or irritation of the eye, or if the condition worsens or persists for more than 72 hours.

KEEP OUT OF REACH OF CHILDREN

Keep out of the reach of children. If swallowed, get medical help or contact a Poison Control Center right away.

Directions

Pull down lower lid of the affected eye(s) and apply small amount (one-fourth inch) of ointment to the inside of the eyelid, one or more times daily, or as directed by a doctor.

Other information

- Store at 20° to 25°C (68° to 77°F)
  [see USP controlled Room Temperature].
- Store away from heat.
- Protect from freezing.
- Keep tightly closed.
- See crimp for Control Number and Expiration Date.
- RETAIN THIS CARTON FOR FUTURE REFERENCE.

Inactive ingredient

Lanolin 2%

Principal Display Panel Text for Container Label:

NDC 13985-600-03

Apexa logo

Artificial Tears STERILE

Ophthalmic Lubricant Ointment

Prevents Irritation and Relieves Dryness of the eye

Can be used at bedtime

AP 704001 Net Weight: 3.5g (1/8 oz)

Principal Display Panel Text for Carton Label:

NDC 13985-600-03

Artificial Tears

Ophthalmic

Lubricant

Ointment

STERILE

Prevents Irritation

and Relieves

Dryness of the eye

Can be used

at bedtime

Apexa logo

AP 704001

Net Weight: 3.5g (1/8 oz)